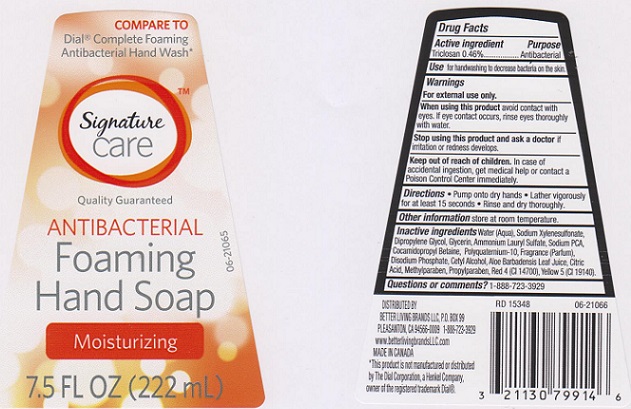 DRUG LABEL: Signature Care Antibacterial Foaming Moisturizing
NDC: 21130-177 | Form: SOAP
Manufacturer: SAFEWAY INC
Category: otc | Type: HUMAN OTC DRUG LABEL
Date: 20160212

ACTIVE INGREDIENTS: TRICLOSAN 4.6 mg/1 mL
INACTIVE INGREDIENTS: WATER; SODIUM XYLENESULFONATE; DIPROPYLENE GLYCOL; GLYCERIN; AMMONIUM LAURYL SULFATE; SODIUM PYRROLIDONE CARBOXYLATE; COCAMIDOPROPYL BETAINE; POLYQUATERNIUM-10 (400 CPS AT 2%); SODIUM PHOSPHATE, DIBASIC ANHYDROUS; CETYL ALCOHOL; ALOE VERA LEAF; CITRIC ACID MONOHYDRATE; METHYLPARABEN; PROPYLPARABEN; FD&C RED NO. 4; FD&C YELLOW NO. 5

DRUG FACTS

Active ingredient

Triclosan 0.46%

Purpose

Antibacterial

Uses

for handwashing to decrease bacteria on the skin.

Warnings

For external use only.

When using this product

avoid contact with eyes. If eye contact occurs, rinse thoroughly with water.

Stop using this product and ask a doctor if

irritaiton or redness develops

Keep out of reach of children.

In case of accidental ingestion, get medical help or contact a Poison Control Center immediately.

Directions

- Pump onto dry hands.
- Lather vigorously for at least 15 seconds.
- Rinse and dry thoroughly.

Other information

store at room temperature

Inactive ingredients

Water (Aqua), Sodium Xylenesulfonate, Dipropylene Glycol, Glycerin, Ammonium Lauryl Sulfate, Sodium PCA, Cocamidopropyl Betaine, Polyquaternium-10, Fragrance (Parfum), Disodium Phosphate, Cetyl Alcohol, Aloe Barbadensis Leaf Juice, Citric Acid, Methylparaben, Propylparaben, Red 4 (CI 14700), Yellow 5 (CI 19140).

Questions or comments?

1-888-723-3929